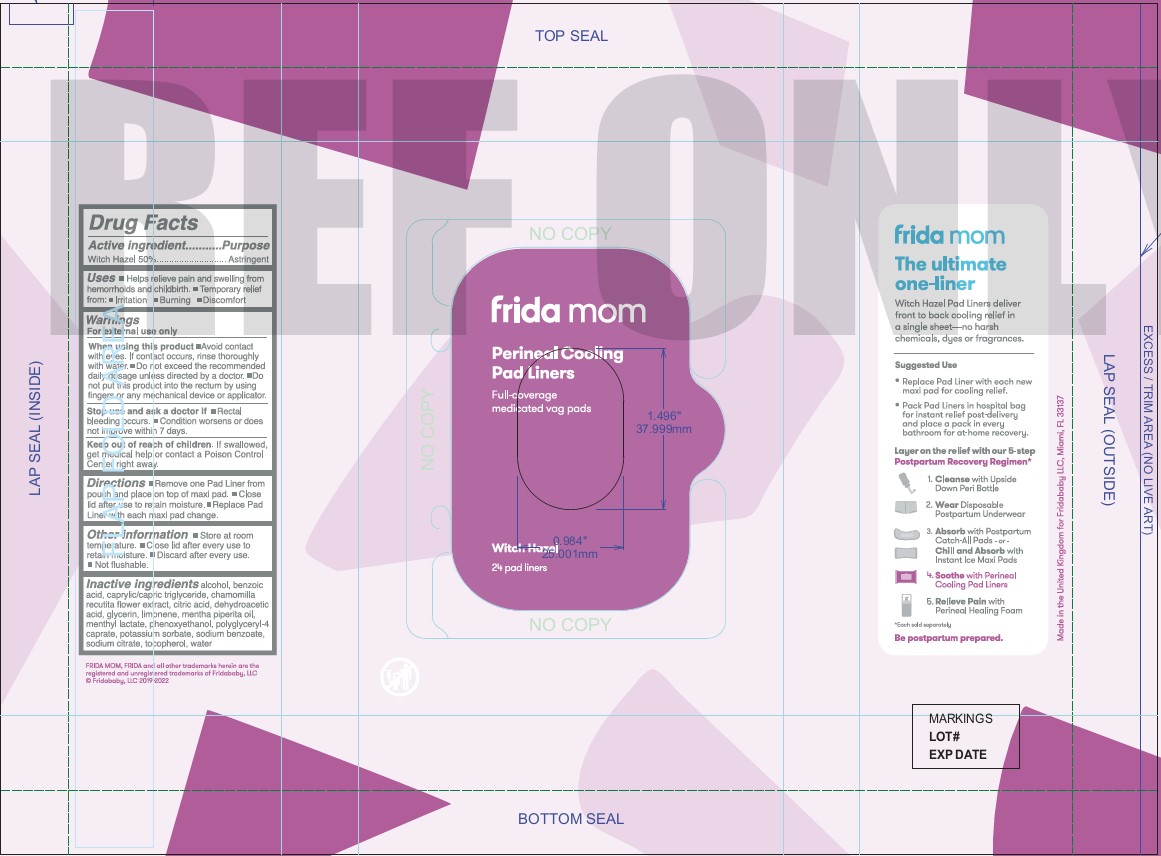 DRUG LABEL: Perineal Cooling Pad Liners
NDC: 72705-420 | Form: SWAB
Manufacturer: Fridababy, LLC
Category: otc | Type: HUMAN OTC DRUG LABEL
Date: 20260204

ACTIVE INGREDIENTS: WITCH HAZEL 50 g/100 g
INACTIVE INGREDIENTS: ALCOHOL 8.824 g/100 g; ANHYDROUS CITRIC ACID 0.016 g/100 g; DEHYDROACETIC ACID 0.11 g/100 g; SODIUM BENZOATE 0.3 g/100 g; MEDIUM-CHAIN TRIGLYCERIDES 0.08 g/100 g; .ALPHA.-TOCOPHEROL, DL- 0.05 g/100 g; PHENOXYETHANOL 0.715 g/100 g; WATER 29.967 g/100 g; MENTHYL LACTATE, (-)- 0.1 g/100 g; GLYCERIN 8.0035 g/100 g; POLYGLYCERYL-4 CAPRATE 1.494 g/100 g; POTASSIUM SORBATE 0.0002 g/100 g; PEPPERMINT OIL 0.04 g/100 g; BENZOIC ACID 0.275 g/100 g; MATRICARIA CHAMOMILLA FLOWERING TOP 0.0175 g/100 g; ANHYDROUS TRISODIUM CITRATE 0.02 g/100 g

Frida Mom – Perineal Cooling Pad Liners

ACTIVE INGREDIENT

Witch Hazel 50% w/w. Purpose: Astringent

PURPOSE

USES: Helps relieve pain and swelling from hemorrhoids and childbirth.

Temporary relief from:

- Irritation
- Burning
- Discomfort

WARNINGS

For external use only.

When using this product:

- Avoid contact with eyes. If contact occurs, rinse thoroughly with water.
- Do not exceed the recommended daily dosage unless directed by a doctor.
- Do not put this product into the rectum by using fingers or any mechanical device or applicator.

Stop use and ask a doctor if:

- Rectal bleeding occurs.
- Condition worsens or does not improve within 7 days.

Keep out of reach of children. If swallowed, get medical help or contact a Poison Control Center right away.

Directions

- Remove one Pad Liner from pouch and place on top of maxi pad.
- Close lid after use to retain moisture.
- Replace Pad Liner with each maxi pad change.

DOSAGE AND ADMINISTRATION

Not required.

OTHER SAFETY INFORMATION

- Store at room temperature.
- Close lid after every use to retain moisture.
- Discard after every use.
- Not flushable.

INACTIVE INGREDIENT

alcohol, benzoic acid, caprylic/capric triglyceride, chamomilla recutita flower extract, citric acid,dehydroacetic acid, glycerin, limonene, mentha piperita oil, menthyl lactate, phenoxyethanol, polyglyceryl-4 caprate, potassium sorbate, sodium benzoate, sodium citrate, tocopherol, water

Package Label - Principal Display Panel.

24 Liners. NDC: 72705-0420-1.